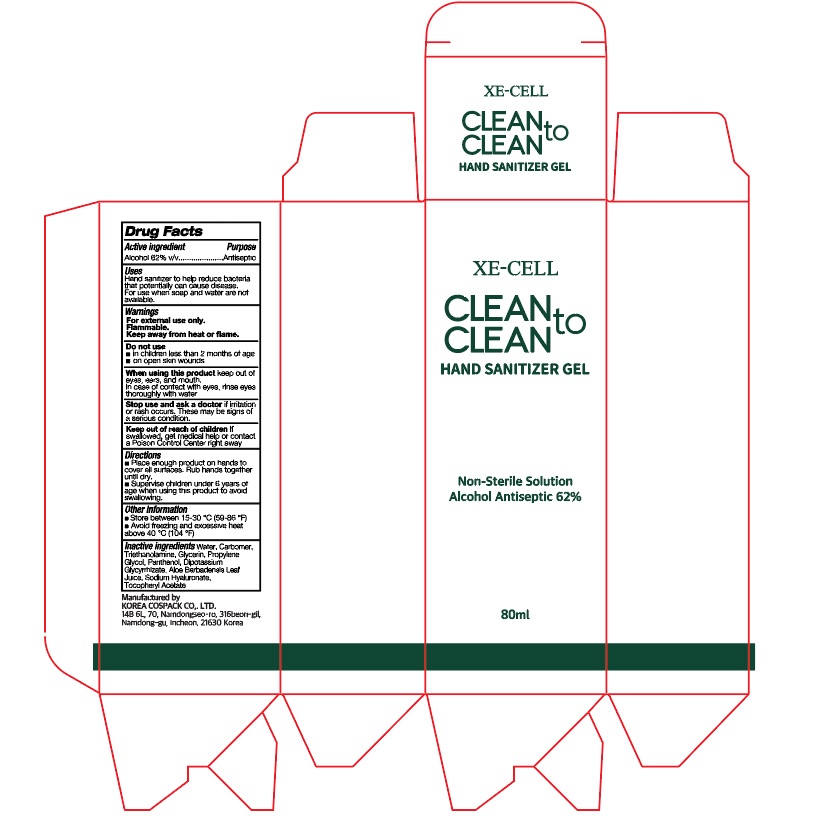 DRUG LABEL: XE-CELL CLEAN TO CLEAN HAND SANITIZER Gel
NDC: 74064-8062 | Form: GEL
Manufacturer: KOREA COSPACK CO.,LTD.
Category: otc | Type: HUMAN OTC DRUG LABEL
Date: 20200517

ACTIVE INGREDIENTS: ALCOHOL 49.6 mL/80 mL
INACTIVE INGREDIENTS: GLYCERIN; CARBOMER HOMOPOLYMER, UNSPECIFIED TYPE; WATER; PROPYLENE GLYCOL; PANTHENOL; GLYCYRRHIZINATE DIPOTASSIUM; ALOE VERA LEAF; .ALPHA.-TOCOPHEROL ACETATE; HYALURONATE SODIUM; TROLAMINE

XE-CELL CLEAN TO CLEAN HAND SANITIZER GEL 80ml Tube + Outer box